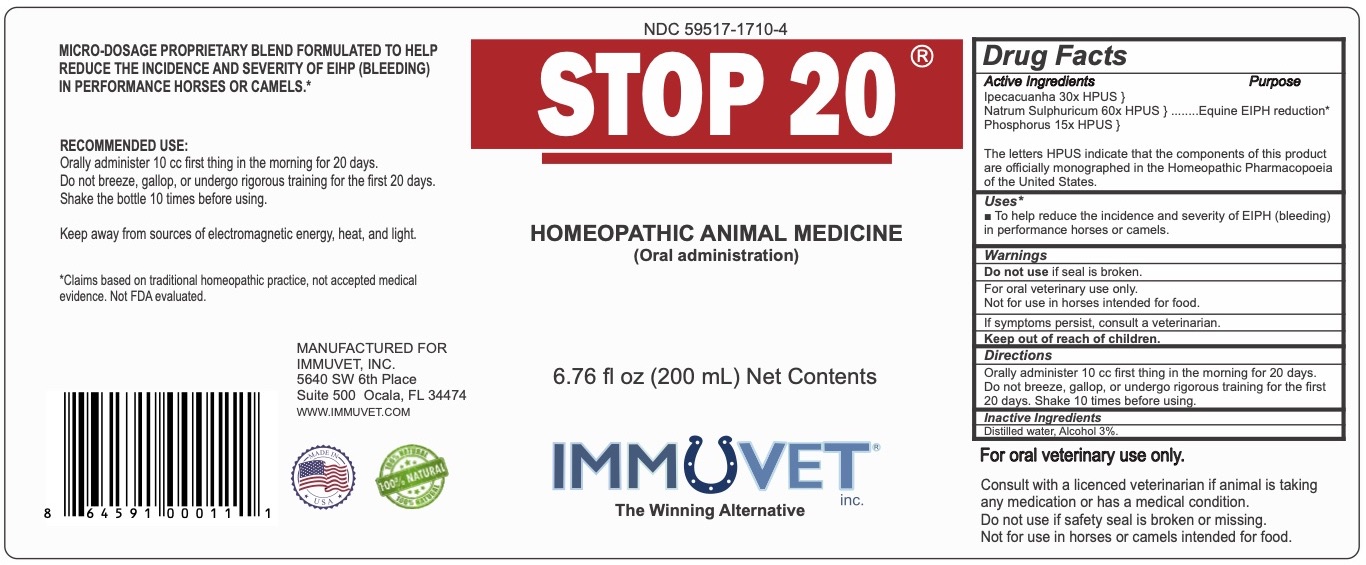 DRUG LABEL: Stop 20
NDC: 59517-1710 | Form: LIQUID
Manufacturer: Immuvet, Inc.
Category: homeopathic | Type: OTC ANIMAL DRUG LABEL
Date: 20251104

ACTIVE INGREDIENTS: IPECAC 30 [hp_X]/1 mL; SODIUM SULFATE 60 [hp_X]/1 mL; PHOSPHORUS 15 [hp_X]/1 mL
INACTIVE INGREDIENTS: ALCOHOL; WATER

Stop 20

PURPOSE

ACCORDING TO HOMEOPATHIC INDICATIONS, THE ACTIVE INGREDIENTS MAY HELP TO REDUCE THE INCIDENCE AND SEVERITY OF EIPH (BLEEDING) IN PERFORMANCE HORSES.**

DIRECTIONS

RECOMMENDED USE:
0cc first thing in the morning for 20 days. Avoid exertion for the first ten days of use.
Keep away from sources of energy, heat and light.

ACTIVE INGREDIENTS

Ipecacuanha 30xv
Natrum Sulphuricum 60x
Phosphorus 15x, 200x

INACTIVE INGREDIENTS

Distilled water, Alcohol 5%

WARNINGS

Do not use if seal is broken.
For Oral Veterinary Use Only.
Not for use in Horses intended for food.
If problems persist, contact a veterinarian.
Keep out of reach of children.

OTHER INFORMATION

**THESE STATEMENTS HAVE NOT BEEN EVALUATED BY THE FDA.
THIS PRODUCT IS NOT INTENDED TO DIAGNOSE, TREAT, CURE OR PREVENT ANY DISEASE.